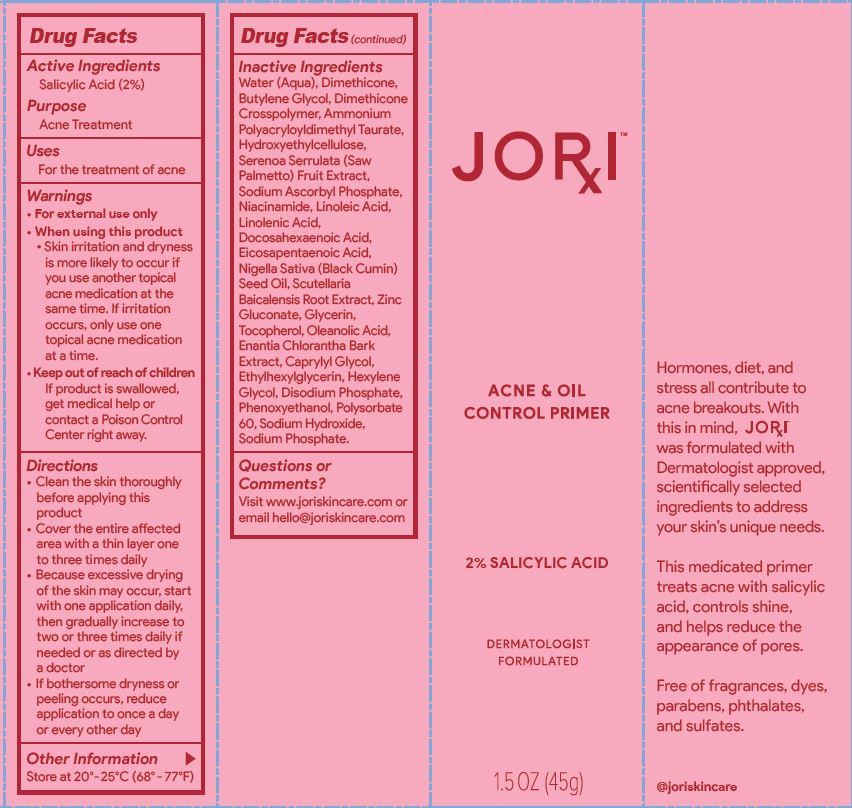 DRUG LABEL: Acne Oil Control Primer
NDC: 62742-4211 | Form: LIQUID
Manufacturer: Allure Labs
Category: otc | Type: HUMAN OTC DRUG LABEL
Date: 20241209

ACTIVE INGREDIENTS: SALICYLIC ACID 20 mg/1 g
INACTIVE INGREDIENTS: SCUTELLARIA BAICALENSIS ROOT; ANNICKIA CHLORANTHA BARK; PHENOXYETHANOL; AMMONIUM POLYACRYLOYLDIMETHYL TAURATE (55000 MPA.S); SAW PALMETTO; DIMETHICONE CROSSPOLYMER (450000 MPA.S AT 12% IN CYCLOPENTASILOXANE); NIACINAMIDE; DOCONEXENT; NIGELLA SATIVA SEED OIL; SODIUM ASCORBYL PHOSPHATE; ZINC GLUCONATE; TOCOPHEROL; ETHYLHEXYLGLYCERIN; POLYSORBATE 60; WATER; DIMETHICONE; BUTYLENE GLYCOL; SODIUM PHOSPHATE, MONOBASIC; CAPRYLYL GLYCOL; SODIUM PHOSPHATE, DIBASIC, ANHYDROUS; SODIUM HYDROXIDE; ICOSAPENT; GLYCERIN; OLEANOLIC ACID; HEXYLENE GLYCOL; HYDROXYETHYL CELLULOSE, UNSPECIFIED; LINOLEIC ACID; LINOLENIC ACID

Drug Facts

Active Ingredients

Salicylic Acid 2 %

Purpose
Acne Treatment

Uses
For the treatment of acne

Warnings

For external use only

Do not use

If irritation occurs

When using this product

Skin irritation and dryness
is more likely to occur if
you use another topical
acne medication at the
same time. If irritation
occurs, only use one
topical acne medication
at a time.

STOP USE

If bothersome dryness or
peeling occurs,

Keep out of reach of children

If product is swallowed,
get medical help or
contact a Poison Control
Center right away.

Directions
Clean the skin thoroughly
before applying this
product
Cover the entire affected
area with a thin layer one
to three times daily
Because excessive drying
of the skin may occur, start
with one application daily,
then gradually increase to
two or three times daily if
needed or as directed by
a doctor
If bothersome dryness or
peeling occurs, reduce
application to once a day
or every other day

Other Information

Store at 20°- 25°C (68° - 77°F)

Inactive Ingredients
Water (Aqua), Dimethicone,
Butylene Glycol, Dimethicone
Crosspolymer, Ammonium
Polyacryloyldimethyl Taurate,
Hydroxyethylcellulose,
Serenoa Serrulata (Saw
Palmetto) Fruit Extract,
Sodium Ascorbyl Phosphate,
Niacinamide, Linoleic Acid,
Linolenic Acid,
Docosahexaenoic Acid,
Eicosapentaenoic Acid,
Nigella Sativa (Black Cumin)
Seed Oil, Scutellaria
Baicalensis Root Extract, Zinc
Gluconate, Glycerin,
Tocopherol, Oleanolic Acid,
Enantia Chlorantha Bark
Extract, Caprylyl Glycol,
Ethylhexylglycerin, Hexylene
Glycol, Disodium Phosphate,
Phenoxyethanol, Polysorbate
60, Sodium Hydroxide,
Sodium Phosphate.